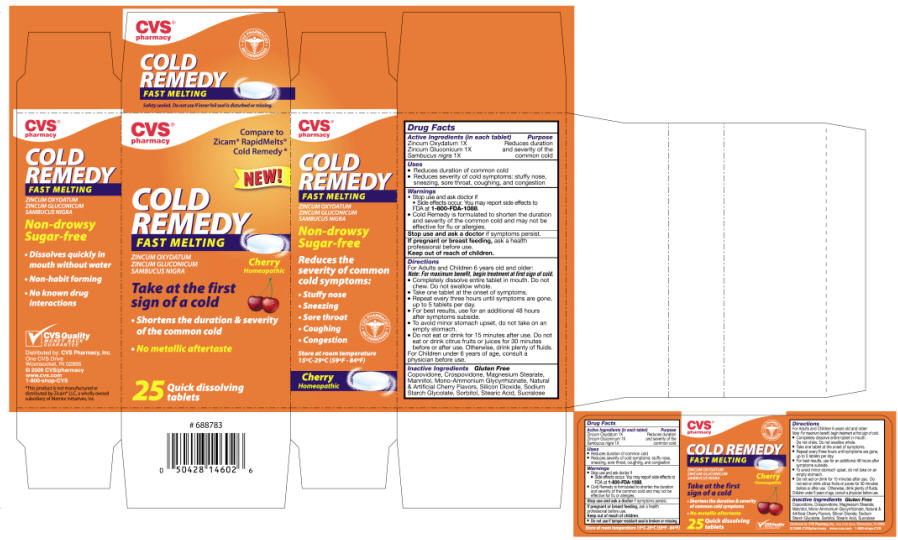 DRUG LABEL: NBB Cherry
NDC: 64762-861 | Form: TABLET, ORALLY DISINTEGRATING
Manufacturer: Dynamic Pharmaceuticals Inc.
Category: homeopathic | Type: HUMAN OTC DRUG LABEL
Date: 20100105

ACTIVE INGREDIENTS: Zinc Gluconate 1 [hp_X]/1 1; Zinc Oxide 1 [hp_X]/1 1; Sambucus Nigra Flower 1 [hp_X]/1 1

CVS®
pharmacy

Drug Facts

ACTIVE INGREDIENT

Active Ingredients (in each tablet) | Purpose
Zincum Oxydatum 1X | Reduces duration
Zincum Gluconicum 1X | and severity of the
Sambucus nigra 1X | common cold

Uses

- Reduces duration of common cold
- Reduces severity of cold symptoms: stuffy nose, sneezing, sore throat, coughing, and congestion

Warnings

- Stop use and ask doctor if
  - Side effects occur. You may report side effects to FDA at 1-800-FDA-1088.
- Cold Remedy is formulated to shorten the duration and severity of the common cold and may not be effective for flu or allergies.

Stop use and ask a doctor if symptoms persist.

PREGNANCY OR BREAST FEEDING

If pregnant or breast feeding, ask a health professional before use.

Keep out of reach of children.

Directions

For Adults and Children 6 years old and older:
Note: For maximum benefit, begin treatment at first sign of cold.

- Completely dissolve entire tablet in mouth. Do not chew. Do not swallow whole.
- Take one tablet at the onset of symptoms.
- Repeat every three hours until symptoms are gone, up to 5 tablets per day.
- For best results, use for an additional 48 hours after symptoms subside.
- To avoid minor stomach upset, do not take on an empty stomach.
- Do not eat or drink for 15 minutes after use. Do not eat or drink citrus fruits or juices for 30 minutes before or after use. Otherwise, drink plenty of fluids.

For Children under 6 years of age, consult a physician before use.

Inactive Ingredients

Gluten Free

Copovidone, Crospovidone, Magnesium Stearate, Mannitol, Mono-Ammonium Glycyrrhizinate, Natural & Artificial Cherry Flavors, Silicon Dioxide, Sodium Starch Glycolate, Sorbitol, Stearic Acid, Sucralose

Distributed by: CVS Pharmacy, Inc.
One CVS Drive
Woonsocket, RI 02895

PRINCIPAL DISPLAY PANEL - 25 tablet carton

CVS®
pharmacy

Compare to
Zicam® RapidMelts®
Cold Remedy*

NEW!

COLD
REMEDY
FAST MELTING

ZINCUM OXYDATUM
ZINCUM GLUCONICUM
SAMBUCUS NIGRA

Cherry
Homeopathic

Take at the first
sign of a cold

- Shortens the duration & severity
  of the common cold
- No metallic aftertaste

25
Quick dissolving
tablets